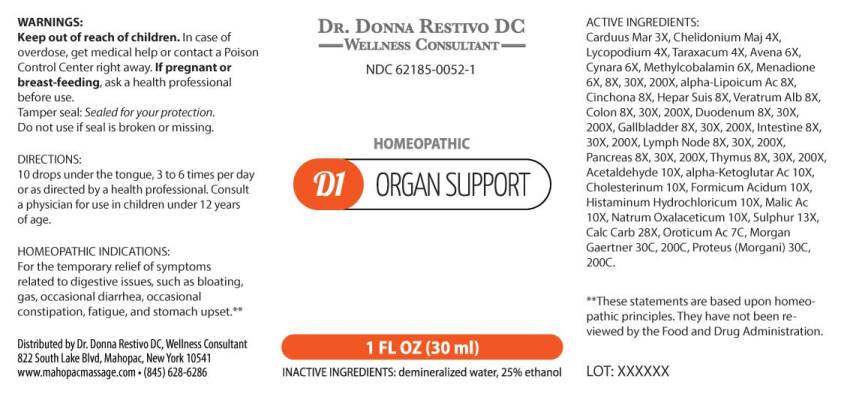 DRUG LABEL: D1 Organ Support
NDC: 62185-0052 | Form: LIQUID
Manufacturer: Dr. Donna Restivo DC
Category: homeopathic | Type: HUMAN OTC DRUG LABEL
Date: 20240118

ACTIVE INGREDIENTS: MILK THISTLE 3 [hp_X]/1 mL; CHELIDONIUM MAJUS WHOLE 4 [hp_X]/1 mL; LYCOPODIUM CLAVATUM SPORE 4 [hp_X]/1 mL; TARAXACUM OFFICINALE 4 [hp_X]/1 mL; AVENA SATIVA FLOWERING TOP 6 [hp_X]/1 mL; CYNARA SCOLYMUS LEAF 6 [hp_X]/1 mL; METHYLCOBALAMIN 6 [hp_X]/1 mL; MENADIONE 6 [hp_X]/1 mL; .ALPHA.-LIPOIC ACID 8 [hp_X]/1 mL; CINCHONA OFFICINALIS BARK 8 [hp_X]/1 mL; PORK LIVER 8 [hp_X]/1 mL; VERATRUM ALBUM ROOT 8 [hp_X]/1 mL; SUS SCROFA COLON 8 [hp_X]/1 mL; SUS SCROFA DUODENUM 8 [hp_X]/1 mL; SUS SCROFA GALLBLADDER 8 [hp_X]/1 mL; PORK INTESTINE 8 [hp_X]/1 mL; SUS SCROFA LYMPH 8 [hp_X]/1 mL; SUS SCROFA PANCREAS 8 [hp_X]/1 mL; SUS SCROFA THYMUS 8 [hp_X]/1 mL; ACETALDEHYDE 10 [hp_X]/1 mL; .ALPHA.-KETOGLUTARIC ACID 10 [hp_X]/1 mL; CHOLESTEROL 10 [hp_X]/1 mL; FORMIC ACID 10 [hp_X]/1 mL; HISTAMINE DIHYDROCHLORIDE 10 [hp_X]/1 mL; MALIC ACID 10 [hp_X]/1 mL; SODIUM DIETHYL OXALACETATE 10 [hp_X]/1 mL; SULFUR 13 [hp_X]/1 mL; OYSTER SHELL CALCIUM CARBONATE, CRUDE 28 [hp_X]/1 mL; OROTIC ACID MONOHYDRATE 7 [hp_C]/1 mL; SALMONELLA ENTERICA SUBSP. ENTERICA SEROVAR ENTERITIDIS 30 [hp_C]/1 mL; PROTEUS MORGANII 30 [hp_C]/1 mL
INACTIVE INGREDIENTS: WATER; ALCOHOL

DRUG FACTS:

ACTIVE INGREDIENTS:

Carduus Marianus 3X, Chelidonium Majus 4X, Lycopodium Clavatum 4X, Taraxacum Officinale 4X, Avena Sativa 6X, Cynara Scolymus 6X, Methylcobalamin 6X, Menadione 6X, 8X, 30X, 200X, Alpha-Lipoicum Acidum 8X, Cinchona Officinalis 8X, Hepar Suis 8X, Veratrum Album 8X, Colon (Suis) 8X, 30X, 200X, Duodenum (Suis) 8X, 30X, 200X, Gallbladder (Suis) 8X, 30X, 200X, Intestine (Suis) 8X, 30X, 200X, Lymph Node (Suis) 8X, 30X, 200X, Pancreas Suis 8X, 30X, 200X, Thymus (Suis) 8X, 30X, 200X, Acetaldehyde 10X, Alpha-Ketoglutaricum Acidum 10X, Cholesterinum 10X, Formicum Acidum 10X, Histaminum Hydrochloricum 10X, Malic Acid 10X, Natrum Oxalaceticum 10X, Sulphur 13X, Calcarea Carbonica 28X, Oroticum Acidum 7C, Morgan Gaertner 30C, 200C, Proteus (Morgani) 30C, 200C.

HOMEOPATHIC INDICATIONS:

For the temporary relief of symptoms related to digestive issues, such as bloating, gas, occasional diarrhea, occasional constipation, fatigue, and stomach upset.**

**These statements are based upon homeopathic principles. They have not been reviewed by the Food and Drug Administration.

WARNINGS:

Keep out of reach of children. In case of overdose, get medical help or contact a Poison Control Center right away.

If pregnant or breast-feeding, ask a health professional before use.

Tamper seal: Sealed for your protection. Do not use if seal is broken or missing.

Keep out of reach of children. In case of overdose, get medical help or contact a Poison Control Center right away.

DIRECTIONS:

10 drops under the tongue, 3 to 6 times per day or as directed by a health professional. Consult a physician for use in children under 12 years of age.

HOMEOPATHIC INDICATIONS:

For the temporary relief of symptoms related to digestive issues, such as bloating, gas, occasional diarrhea, occasional constipation, fatigue, and stomach upset.**

**These statements are based upon homeopathic principles. They have not been reviewed by the Food and Drug Administration.

INACTIVE INGREDIENTS:

demineralized Water, 25% ethanol

QUESTIONS:

Distributed by Dr. Donna Restivo DC, Wellness Consultant

822 South Lake Blvd, Mahopac, New York 10541

www.mahopacmassage.com • (845) 628-6286

PACKAGE LABEL DISPLAY:

DR. DONNA RESTIVO DC
WELLNESS CONSULTANT
NDC 62185-0052-1
HOMEOPATHIC
D1 ORGAN SUPPORT
1 FL OZ (30 ml)